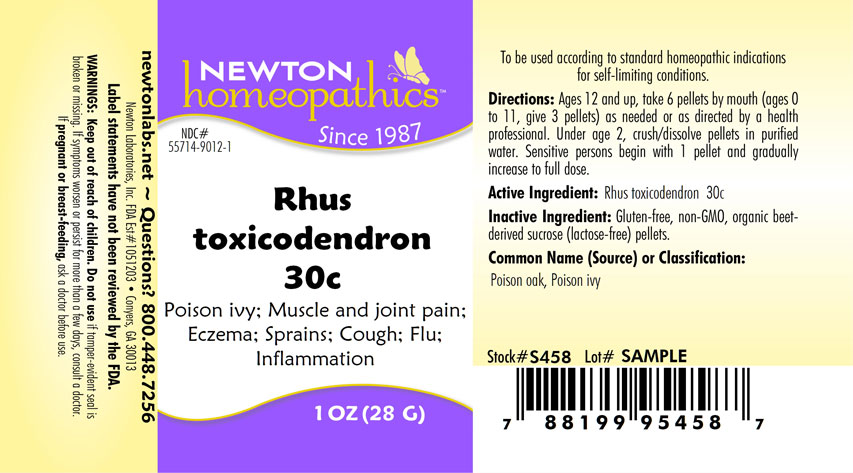 DRUG LABEL: Rhus toxicodendron
NDC: 55714-9012 | Form: PELLET
Manufacturer: Newton Laboratories, Inc.
Category: homeopathic | Type: HUMAN OTC DRUG LABEL
Date: 20250210

ACTIVE INGREDIENTS: TOXICODENDRON PUBESCENS LEAF 30 [hp_C]/1 g
INACTIVE INGREDIENTS: SUCROSE

Rhus 9012P

INDICATIONS & USAGE SECTION

Poison ivy; Muscle and joint pain; Eczema; Sprains; Cough; Flu: Inflammation

DOSAGE & ADMINISTRATION SECTION

Directions: Ages 12 and up, take 6 pellets by mouth, (ages 0 to 11, give 3 pellets) as needed or as directed by a health professional. Under age 2, crush/dissolve pellets in purified water. Sensitive persons begin with 1 pellet and gradually increse to full dose.

OTC - ACTIVE INGREDIENT SECTION

Rhus toxicodendron 30c

OTC - PURPOSE SECTION

Poison ivy; Muscle and joint pain; Eczema; Sprains; Cough; Flu: Inflammation

INACTIVE INGREDIENT SECTION

Inactive Ingredients: Gluten-free, non-GMO, organic beet-derived sucrose (lactose free) pellets

QUESTIONS SECTION

newtonlabs.net – Questions? 800.448.7256

Newton Laboratories, Inc. FDA Est # 1051203 - Conyers, GA 30013

WARNINGS SECTION

Warning: Keep out of reach of children. Do not use if tamper - evident seal is broken or missing. If symptoms worsen or persist for more than a few days, consult a doctor. If pregnant or breast-feeding, ask a doctor before use.

OTC - PREGNANCY OR BREAST FEEDING SECTION

If pregnant or breast-feeding, ask a doctor before use.

OTC - KEEP OUT OF REACH OF CHILDREN SECTION

Keep out of reach of children.